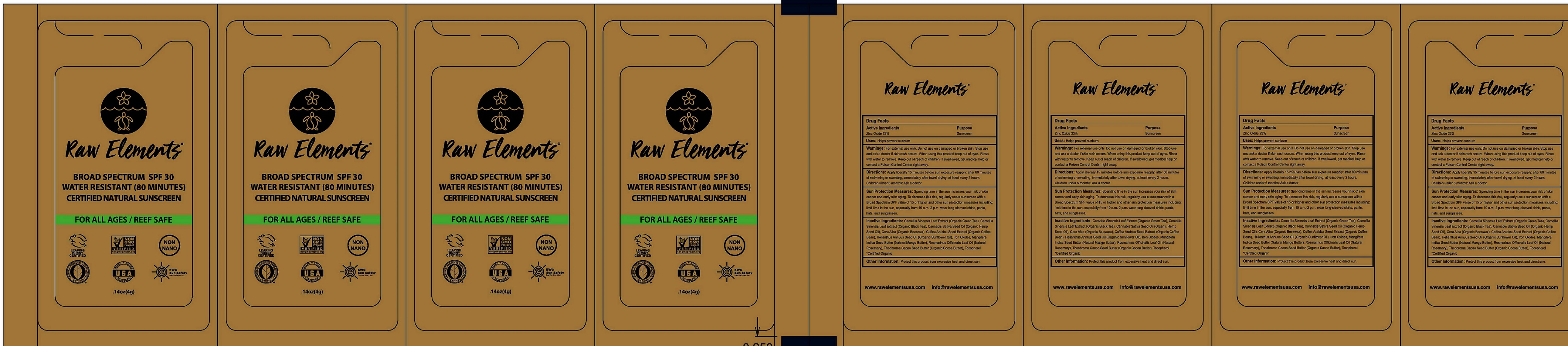 DRUG LABEL: Raw Elements Eco Formula SPF30 Sample Packs
NDC: 70680-308 | Form: LOTION
Manufacturer: Raw Elements LLC
Category: otc | Type: HUMAN OTC DRUG LABEL
Date: 20231208

ACTIVE INGREDIENTS: ZINC OXIDE 230 mg/1 g
INACTIVE INGREDIENTS: GREEN TEA LEAF; WHITE WAX; FERRIC OXIDE RED; MANGIFERA INDICA SEED BUTTER; ROSEMARY OIL; TOCOPHEROL

Raw Elements Eco Lotion Formula SPF30+ Sample Packs

Active Ingredients

Zinc Oxide 23%

Purpose

Sunscreen

Uses:

Helps prevent sunburn

Warnings:

For external use only.

Do not use

on damaged or broken skin.

Stop use and ask a doctor

if skin rash occurs.

When using this product

keep out of eyes. Rinse with water to remove.

Keep out of reach of children.

If swallowed, get medical help or contact a Poison Control Center right away.

Directions:

Apply liberally 15 minutes before sun exposure reapply: after 80 minutes of swimming or sweating, Immediately after towel drying, at least every 2 hours. Children under 6 months: Ask a doctor

Sun Protection Measures: Spending time in the sun increases your risk of skin cancer and early skin aging. To decrease this risk, regularly use a sunscreen with a Broad Spectrum SPF value of 15 or higher and other sun protection measures including: limit time in the sun, especially from 10 a.m.-2 p.m. wear long-sleeved shirts, pants, hats, and sunglasses.

Inactive Ingredients:

Camellia Sinensis Leaf Extract (Organic Green Tea), Camellia Sinensis Leaf Extract (Organaic Black Tea), Cannabis Sativa Seed Oil (Organic Hemp Seed Oil), Cera Alba (Organic Beeswax), Coffea Arabica Seed Extract (Organic Coffee Bean), Helianthus Annuus Seed Oil (Organic Sunflower Oil), Iron Oxides, Mangifera Indica Seed Butter (Natural Mango Butter), Rosmarinus Officinalis Leaf Oil (Natural Rosemary, Theobroma Cacao Seed Butter (Organic Cocoa Butter), Tocopherol
*Certified Organic

Other Information:

Protect this product from excessive heat and direct sun.